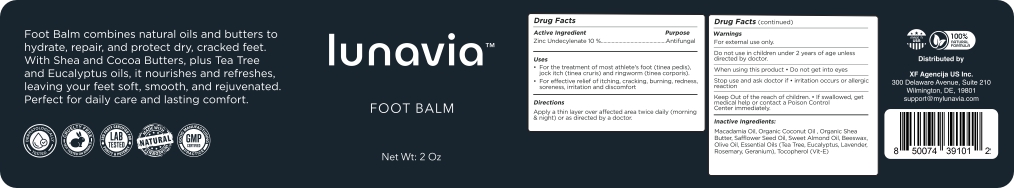 DRUG LABEL: Lunavia Antifungal Foot Balm
NDC: 85210-003 | Form: OINTMENT
Manufacturer: XF Agencija Limited
Category: otc | Type: HUMAN OTC DRUG LABEL
Date: 20250613

ACTIVE INGREDIENTS: ZINC UNDECYLENATE 10 g/100 g
INACTIVE INGREDIENTS: COCONUT OIL; SYNTHETIC BEESWAX; SHEA BUTTER; MACADAMIA OIL; ALPHA-TOCOPHEROL; SAFFLOWER OIL; OLIVE OIL; ROSEMARY OIL; EUCALYPTUS OIL; GERANIUM OIL, ALGERIAN TYPE; ALMOND OIL; TEA TREE OIL; LAVENDER OIL

Lunavia Antifungal Foot Balm

Active Ingredient

Zinc Undecylenate 10%

Purpose

Antifungal

Uses

- For the treatment of most athlete's foot (tinea pedis), jock itch (tinea cruris) and ringworm (tinea corporis).
- For effective relief of itching, cracking, burning, redness, soreness, irritation and discomfort

Directions

Apply a thin layer over affected area twice daily (morning & night) or as directed by a doctor.

Warnings

For External Use only.

Do not use in children under 2 years of age unless directed by doctor.

When using this product

- Do not get into eyes

Stop use and ask doctor if

- irritation occurs or allergic reaction

KEEP OUT OF REACH OF CHILDREN

Keep out of the reach of children. If swallowed, get medical help or contact a poison control center immediately.

Inactive Ingredients

Macadamica Oil, Organic Coconut Oil, Organic Shea Butter, Safflower Seed Oil, Sweet Almond Oil, Beeswax, Olive Oil, Essential Oils (Tea Tree, Eucalyptus, Lavender, Rosemary, Geranium), Tocopherol (Vit-E)